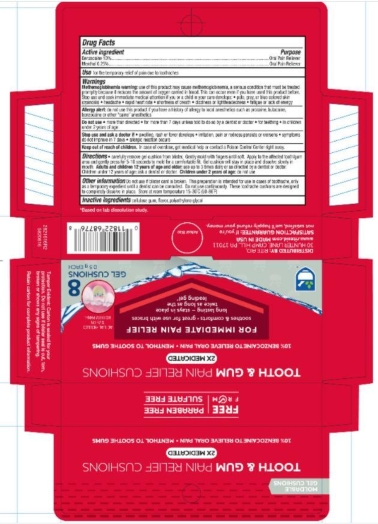 DRUG LABEL: Toothache and Gum Relief Cushions
NDC: 11822-1616 | Form: DRESSING
Manufacturer: Rite Aid
Category: otc | Type: HUMAN OTC DRUG LABEL
Date: 20251121

ACTIVE INGREDIENTS: MENTHOL 0.25 g/100 g; BENZOCAINE 10 g/100 g
INACTIVE INGREDIENTS: POLYETHYLENE GLYCOL 400; POLYETHYLENE GLYCOL 3350; CARBOXYMETHYLCELLULOSE SODIUM, UNSPECIFIED FORM

5820616 RA Tooth Cushions

ACTIVE INGREDIENT

Benzocaine 10% . . . Oral pain reliever

Menthol 0.25% . . . Oral pain reliever

PURPOSE

INDICATIONS AND USAGE

for the temporary relief of pain due to toothaches

WARNINGS

Methemoglobinemia warning: use of this product may cause methemoglobinemia, a serious condition that must be treated promptly because it reduces the amount of oxygen carried in blood. This can occur even if you have used this product before. Stop use and seek immediate medical attention if you or a child in your care develop: * pale, gray, or blue colored skin (cyanosis) * headache * rapid heart rate * shortness of breath * dizziness or lightheadedness * fatigue or lack of energy

Allergy alert: do not use this product if you have a history of allergy to local anesthetics such as procaine, butacaine, benzocaine, or other "caine" anesthetics

Do not use * more than directed * for more than 7 days unless told to do so by a dentist or doctor * for teething * in children under 2 years of age

Stop use and ask a doctor if * swelling, rash or fever develops * iffitation, pain or redness persists or worsens * symptoms do not improve in 7 days * allergic reaction occurs

Keep out of reach of children. In case of overdose, get medical help or contact a Poison Control Center right away.

DOSAGE AND ADMINISTRATION

carefully remove gel cushion from blister. Gently mold with fingers until soft. Apply to the affected tooth/gum area and gently press for 5-10 seconds to mold for a comfortable fit. Gel cushion will stay in place and dissolve slowly in mouth. Adults and children 12 years of age and older: use up to 3 times daily or as directed by a dentist or doctor. Children under 12 years of age: ask a dentist or doctor. Children under 2 years of age: do not use

Do not use if blister card is broken. This preparation is intended for use in cases of toothache, only as a temporary expedient until a dentist can be consulted. Do not use continuously. These toothache cushions are designed to completely dissolve in place. Store at room temperature 15-30°C (59-86°F)

INACTIVE INGREDIENT

cellulose gum, flavor, polyethylene glycol